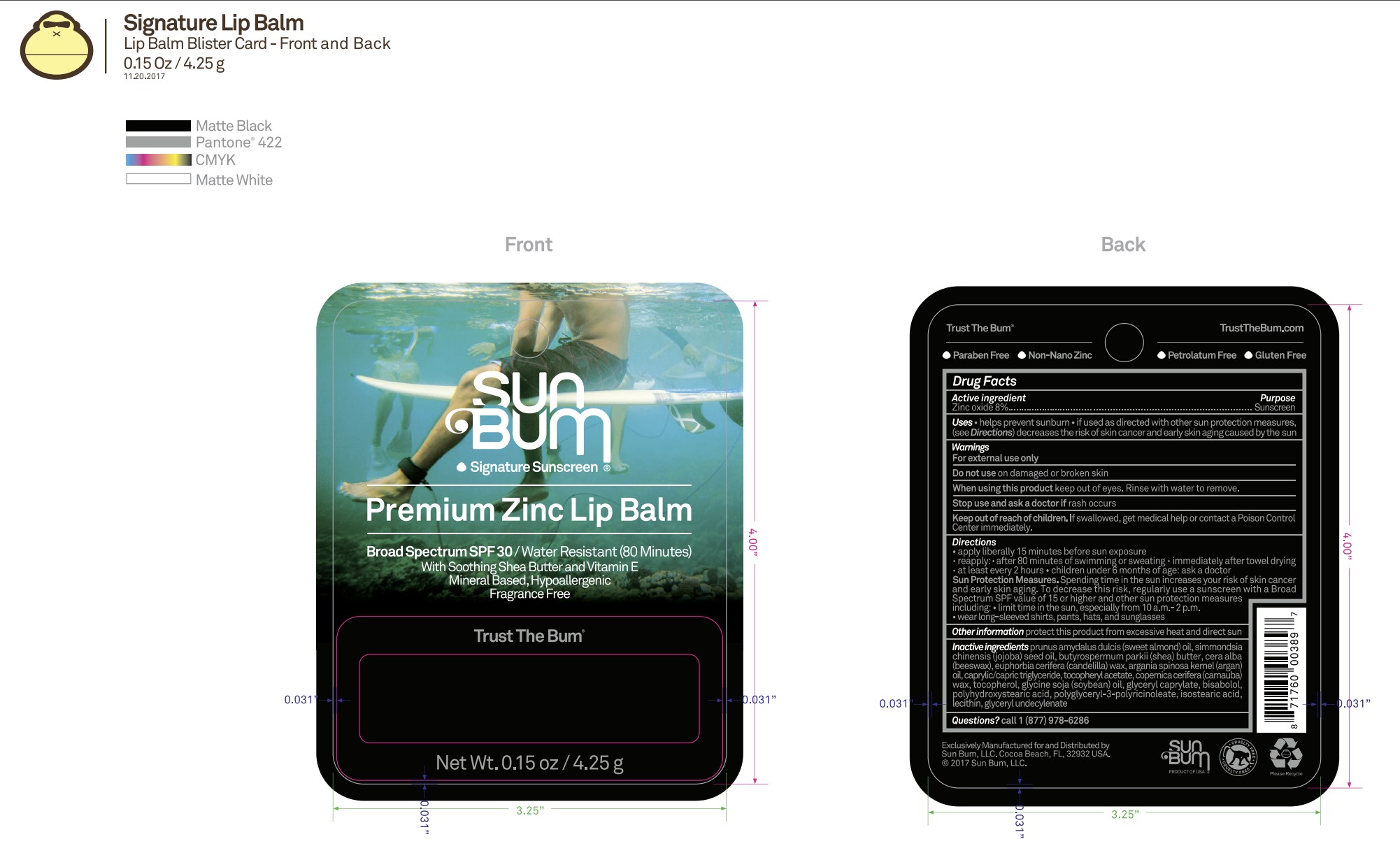 DRUG LABEL: Sun Bum Signature Sunscreen Premium Zinc Lip Balm Broad Spectrum SPF 30
NDC: 69039-802 | Form: STICK
Manufacturer: Sun Bum, LLC
Category: otc | Type: HUMAN OTC DRUG LABEL
Date: 20250818

ACTIVE INGREDIENTS: ZINC OXIDE 80 mg/1 g
INACTIVE INGREDIENTS: LECITHIN, SUNFLOWER; TOCOPHEROL; SOYBEAN OIL; BISABOLOL; CAPRYLIC/CAPRIC TRIGLYCERIDE; .ALPHA.-TOCOPHEROL ACETATE; EUPHORBIA CERIFERA (CANDELILLA) WAX; GLYCERYL CAPRYLATE; BUTYROSPERMUM PARKII (SHEA) BUTTER; POLYGLYCEROL POLYRICINOLEIC ACID; ISOSTEARIC ACID; SIMMONDSIA CHINENSIS (JOJOBA) SEED OIL; PRUNUS AMYGDALUS DULCIS (SWEET ALMOND) OIL; ARGAN OIL; POLYHYDROXYSTEARIC ACID (2300 MW); GLYCERYL 1-UNDECYLENATE; BEESWAX; COPERNICIA CERIFERA (CARNAUBA) WAX

Sun Bum Signature Sunscreen Premium Zinc Lip Balm Broad Spectrum SPF 30

Active ingredients

Zinc Oxide 8%

Purpose

Sunscreen

Uses

• helps prevent sunburn • if used as directed with other sun protection measures, (see Directions) decreases the risk of skin cancer and early skin aging caused by the sun

Warnings

For external use only

Do not use on damaged or broken skin

When using this product keep out of eyes. Rinse with water to remove.

Stop use and ask a doctor if rash occurs

Keep out of reach of children. If swallowed, get medical help or contact a Poison Control Center immediately.

Warnings

Keep Out Of Reach Of Children

Directions

• apply liberally 15 minutes before sun exposure

• reapply: • after 80 minutes of swimming or sweating • immediately after towel drying • at least every 2 hours

• children under 6 months of age: ask a doctor

• Sun Protection Measures. Spending time in the sun increases your risk of skin cancer and early skin aging. To decrease this risk, regularly use a sunscreen with a Broad Spectrum SPF value of 15 or higher and other sun protection measures including:

• limit time in the sun, especially from 10 a.m.- 2 p.m.

• wear long-sleeved shirts, pants, hats and sunglasses

Directions

• shake well before use

• apply liberally 15 minutes before sun exposure

Other Information

protect this product from excessive heat and direct sun

Inactive Ingredients

prunus amydalus dulcis (sweet almond) oil, simmondsia chinensis (jojoba) seed oil, butyrospermum parkii (shea) butter, cera alba (beeswax), euphorbia cerifera (candelilla) wax, argania spinosa kernel (argan) oil, caprylic/capric triglyceride, tocopheryl acetate, copernica cerifera (carnauba) wax, tocopherol, glycine soja (soybean) oil, glyceryl caprylate, bisabolol, polyhydroxystearic acid, polyglyceryl-3-polyrincoleate, isostearic acid, lecithin, glyceryl undecylenate

Questions?

1-877-978-6286